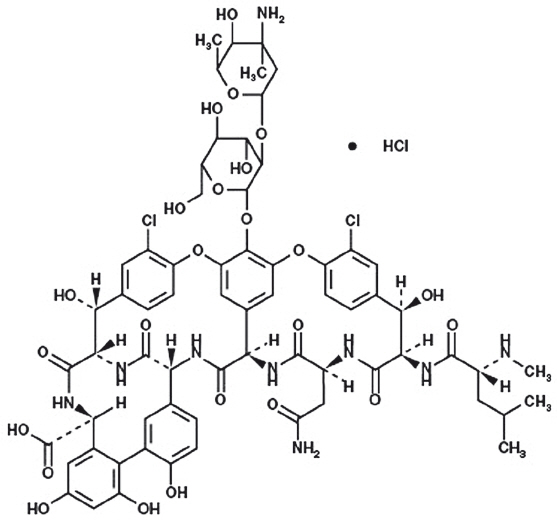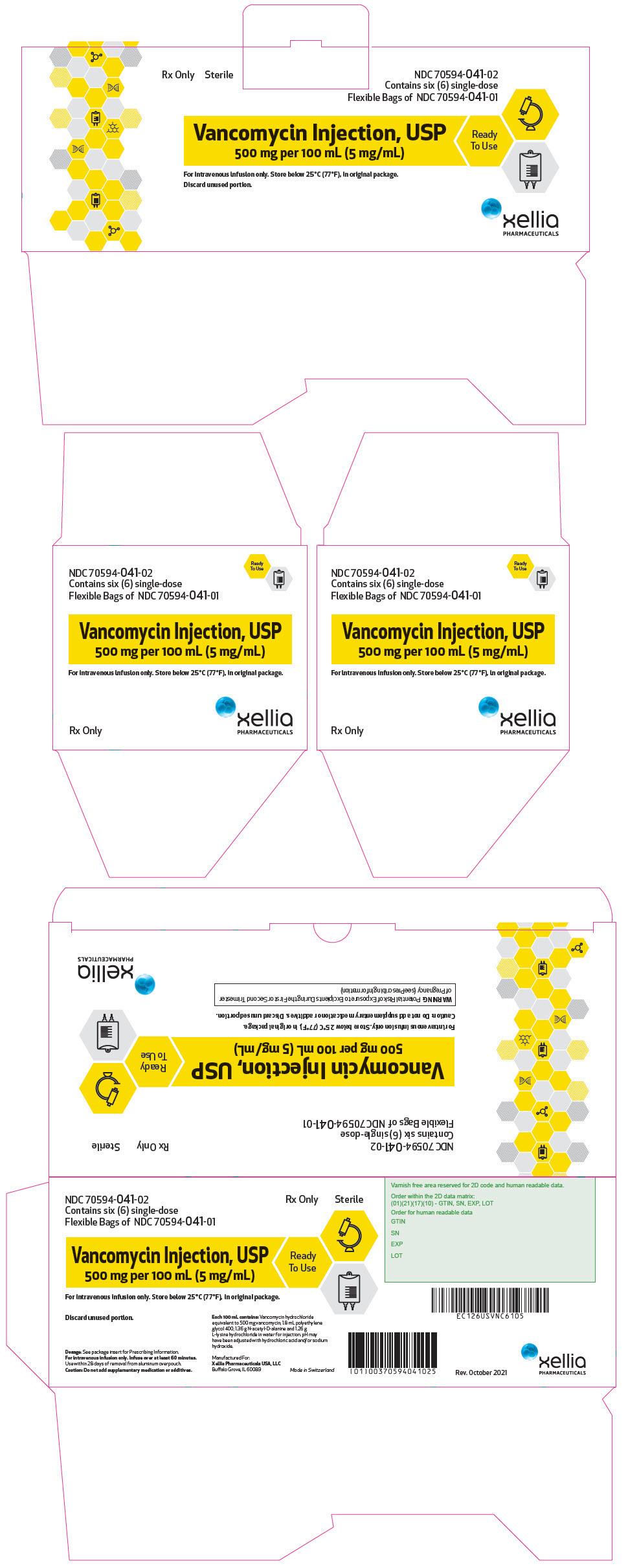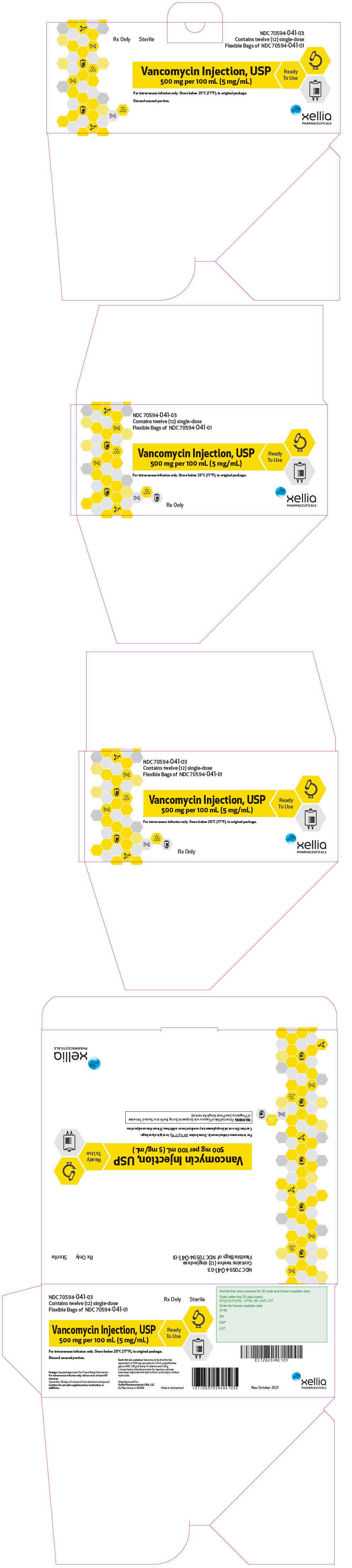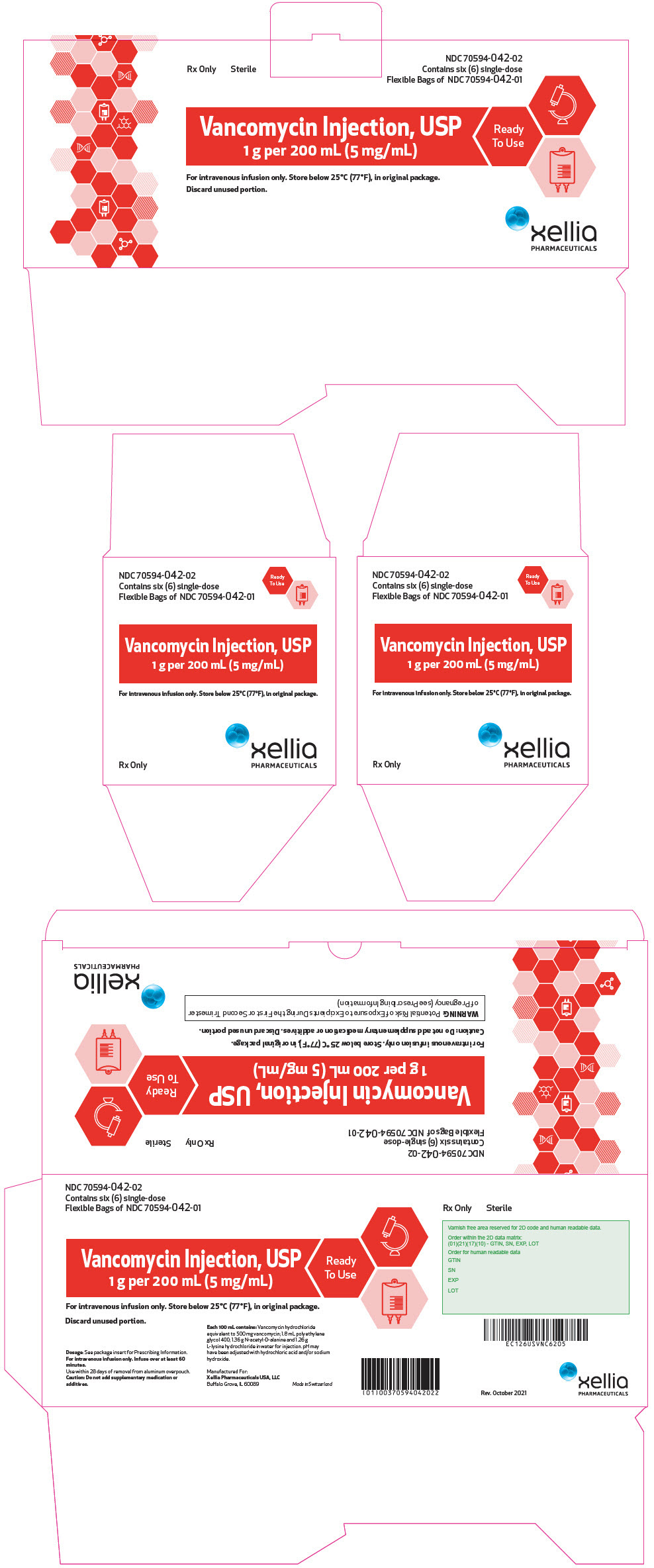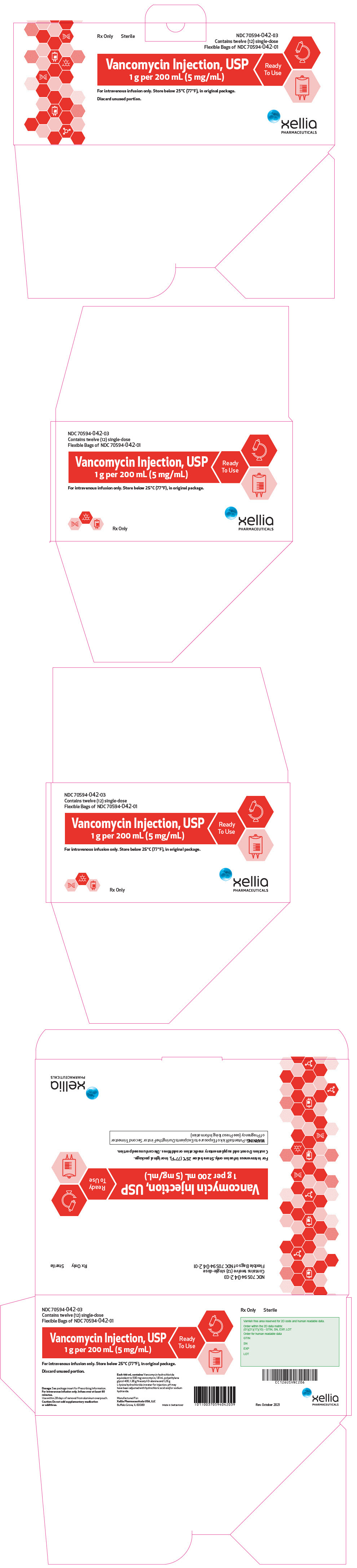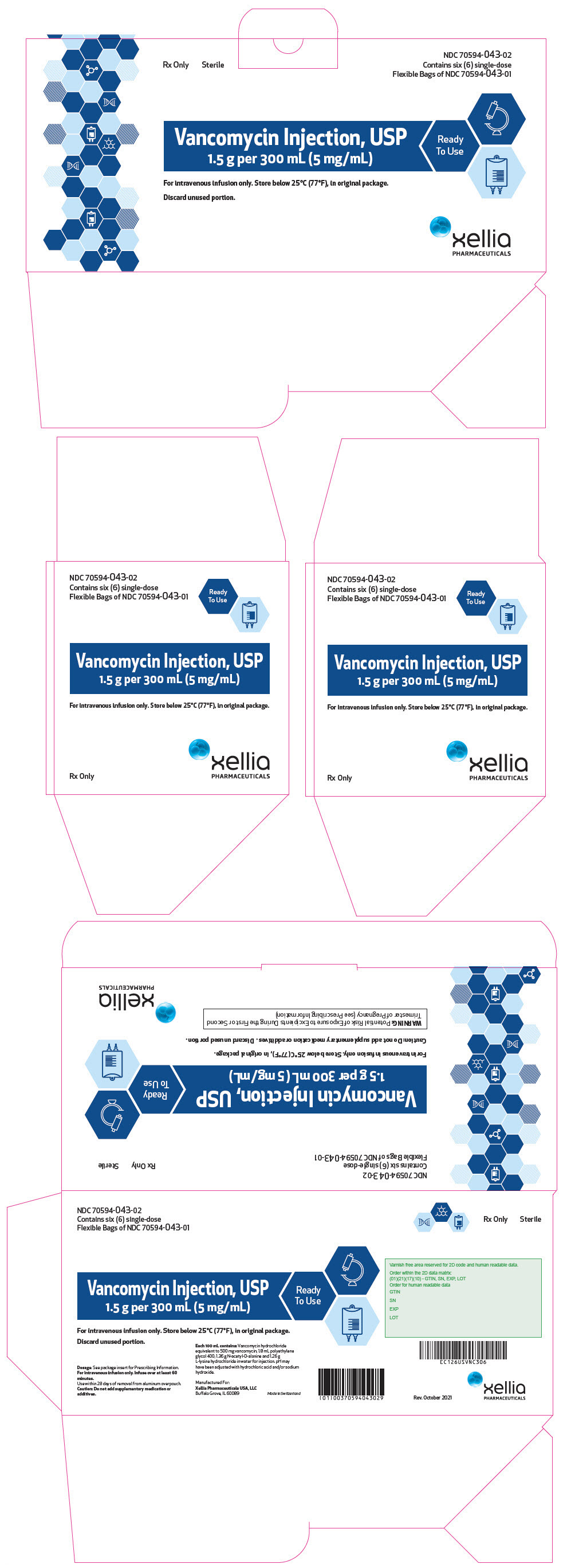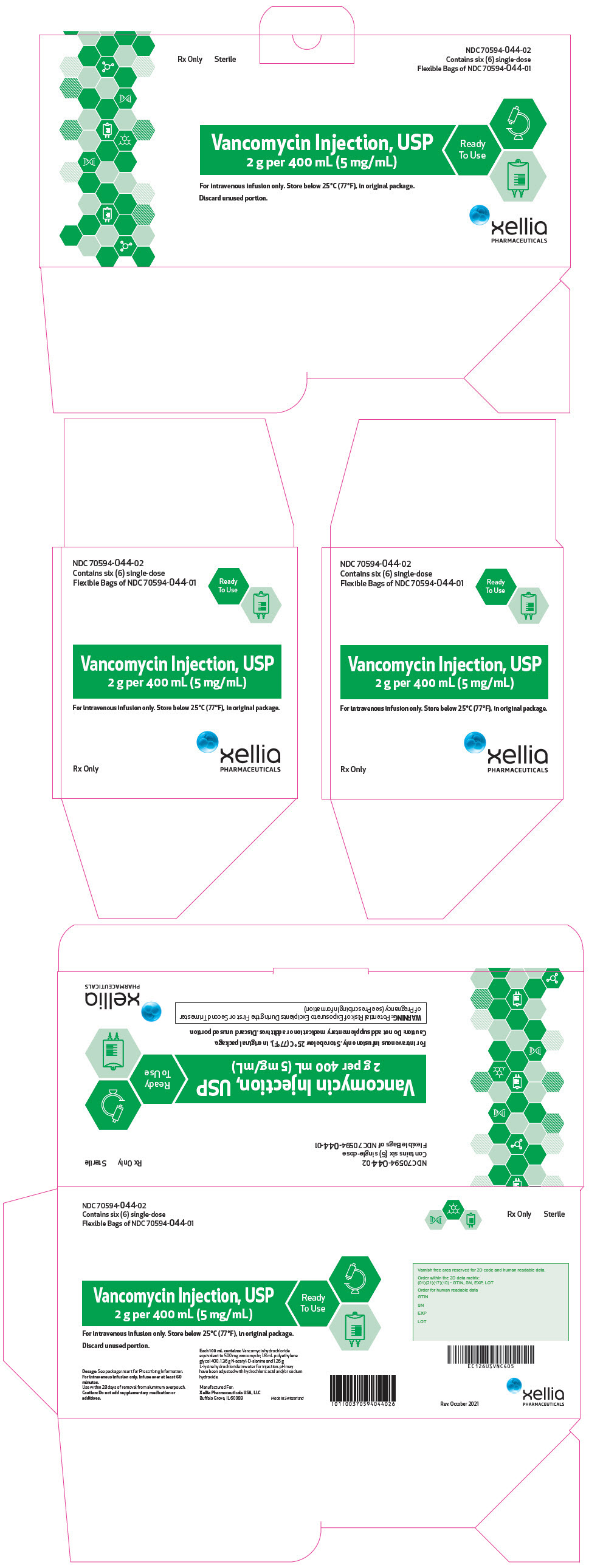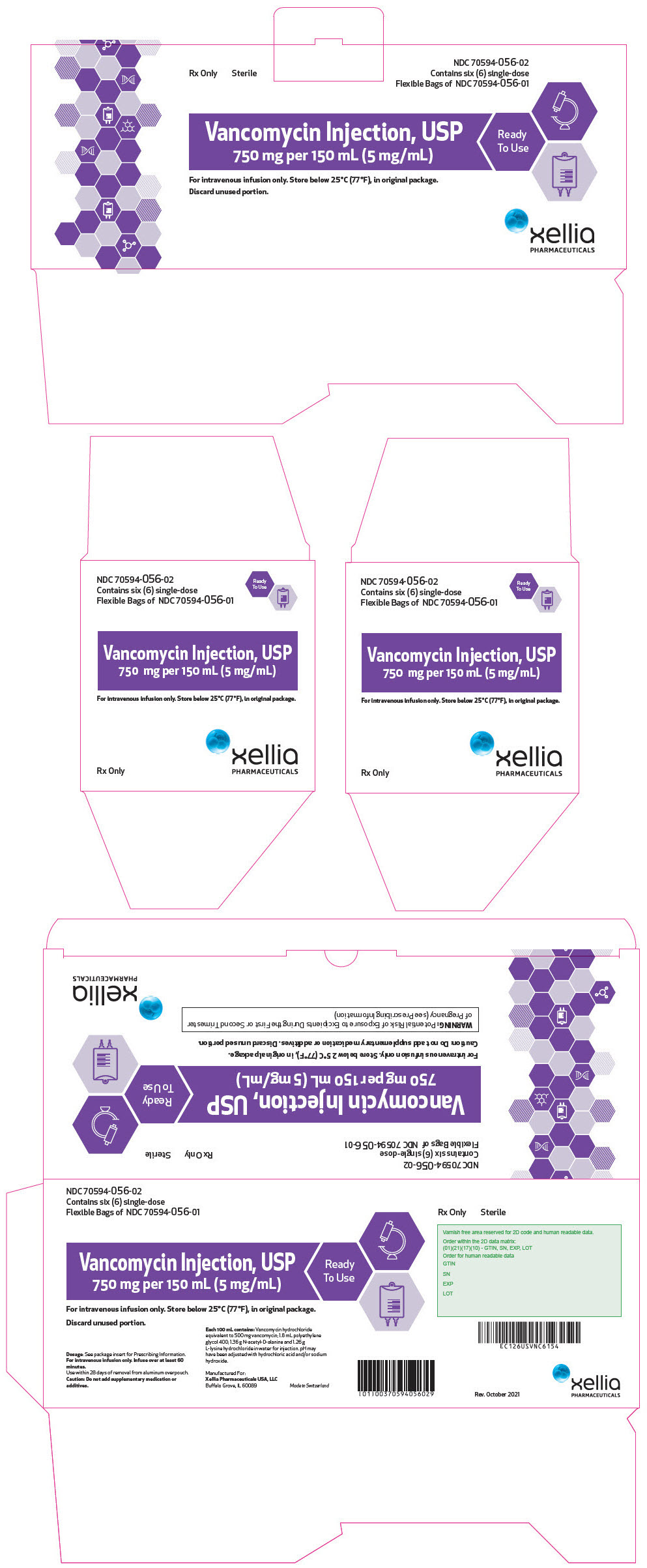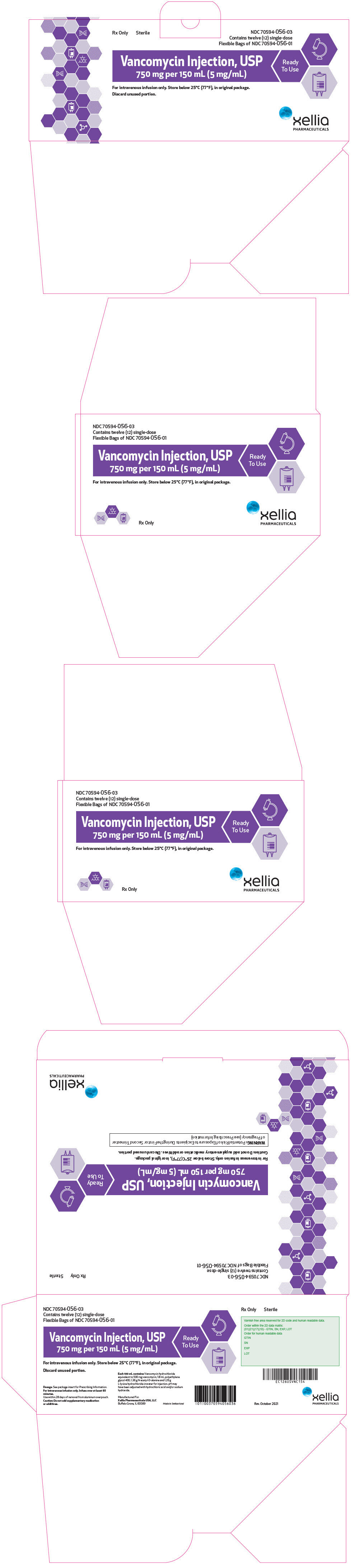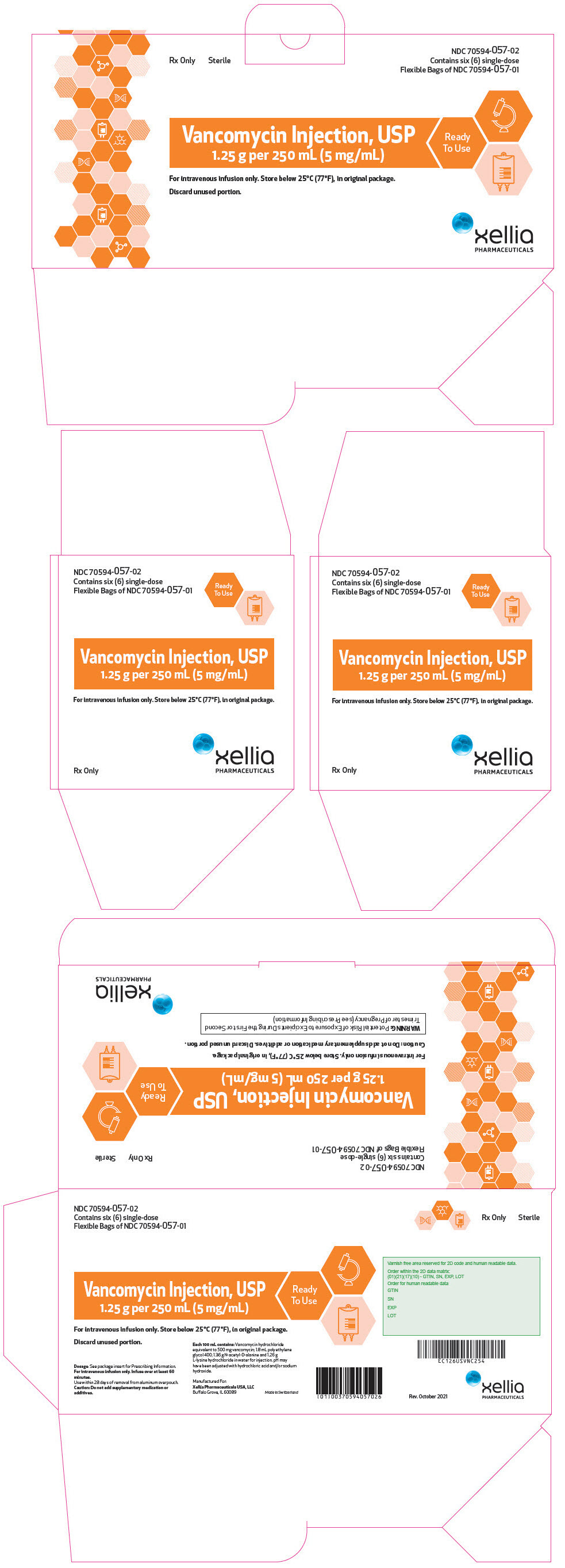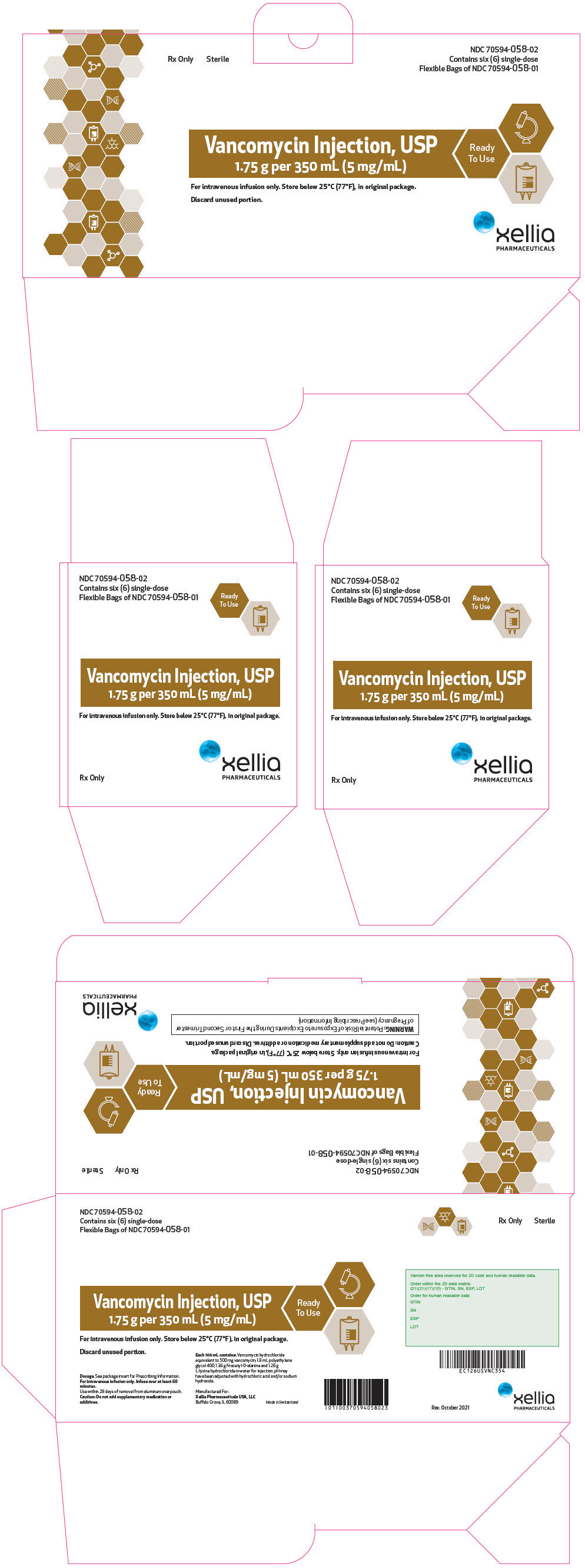 DRUG LABEL: Vancomycin
NDC: 70594-041 | Form: INJECTION, SOLUTION
Manufacturer: Xellia Pharmaceuticals USA LLC
Category: prescription | Type: HUMAN PRESCRIPTION DRUG LABEL
Date: 20230323

ACTIVE INGREDIENTS: VANCOMYCIN 500 mg/100 mL

HIGHLIGHTS OF PRESCRIBING INFORMATION

These highlights do not include all the information needed to use VANCOMYCIN INJECTION, safely and effectively. See full prescribing information for VANCOMYCIN INJECTION.
VANCOMYCIN injection, for intravenous use
Initial U.S. Approval: 1958

RECENT MAJOR CHANGES

Boxed Warning | 10/2021
Warnings and Precautions, Severe Dermatologic Reactions (5.5) | 5/2021
Warnings and Precautions, Potential Risk of Exposure to Excipients During the First or Second Trimester of Pregnancy (5.1) | 10/2021

WARNING: POTENTIAL RISK OF EXPOSURE TO EXCIPIENTS DURING THE FIRST OR SECOND TRIMESTER OF PREGNANCY

See full prescribing information for complete boxed warning.

If use of vancomycin is needed during the first or second trimester of pregnancy, use other available formulations of vancomycin. This formulation of vancomycin injection contains the excipients polyethylene glycol (PEG 400) and N-acetyl D-alanine (NADA), which resulted in fetal malformations in animal reproduction studies at dose exposures approximately 8 and 32 times, respectively, higher than the exposures at the human equivalent dose (5.1, 8.1)

1 INDICATIONS AND USAGE

Vancomycin Injection is a glycopeptide antibacterial indicated in adult and pediatric patients (1 month and older) for the treatment of:

- Septicemia (1.1)
- Infective Endocarditis (1.2)
- Skin and Skin Structure Infections (1.3)
- Bone Infections (1.4)
- Lower Respiratory Tract Infections (1.5)

To reduce the development of drug-resistant bacteria and maintain the effectiveness of Vancomycin Injection and other antibacterial drugs, Vancomycin Injection should be used only to treat or prevent infections that are proven or strongly suspected to be caused by susceptible bacteria. (1.6)

2 DOSAGE AND ADMINISTRATION

- Use this formulation of Vancomycin Injection only in patients who require the entire (500 mg, 750 mg, 1 g, 1.25 g, 1.5 g, 1.75 g or 2 g) dose and not any fraction thereof. (2.1)
- For intravenous use only. Do Not administer orally.
- Administer Vancomycin Injection by intravenous infusion over 60 minutes or greater to reduce the risk of infusion reactions (2.1)
- Adult Patients: 2 g divided either as 0.5 grams (g) every 6 hours or 1 g every 12 hours (2.2)
- Pediatric Patients (1 Month and Older): 10 mg/kg per dose given every 6 hours (2.3)
- Patients with Renal Impairment: See full prescribing information for recommended doses in patients with renal impairment (2.4)
- See full prescribing information for further important administration and preparation instructions (2.1, 2.5)

3 DOSAGE FORMS AND STRENGTHS

Vancomycin Injection, USP: Single-dose flexible bags containing 500 mg vancomycin in 100 mL, 750 mg vancomycin in 150 mL, 1 g vancomycin in 200 mL, 1.25 g vancomycin in 250 mL, 1.5 g vancomycin in 300 mL, 1.75 g vancomycin in 350 mL and 2 g vancomycin in 400 mL of liquid. (3)

4 CONTRAINDICATIONS

Hypersensitivity to vancomycin (4)

5 WARNINGS AND PRECAUTIONS

- Infusion Reactions: Hypotension, including shock and cardiac arrest, wheezing, dyspnea, urticaria, muscular and chest pain and "red man syndrome" which manifests as pruritus and erythema that involves the face, neck and upper torso may occur with rapid intravenous administration. To reduce the risk of infusion reactions, administer Vancomycin Injection over a period of 60 minutes or greater and also prior to intravenous anesthetic agents. (2.1, 5.2)
- Nephrotoxicity: Systemic vancomycin exposure may result in acute kidney injury (AKI) including acute renal failure, mainly due to interstitial nephritis or less commonly acute tubular necrosis. Monitor serum vancomycin concentrations and renal function. (5.3)
- Ototoxicity: Ototoxicity has occurred in patients receiving vancomycin. Monitor for signs and symptoms of ototoxicity during therapy. Monitor serum vancomycin concentrations and renal function. Assessment of auditory function may be appropriate in some instances. (5.4)
- Severe Dermatologic Reactions: Discontinue Vancomycin Injection at the first appearance of skin rashes, mucosal lesions, or blisters. (5.5)
- Clostridioides difficile-Associated Diarrhea: Evaluate patients if diarrhea occurs. (5.6).
- Neutropenia: Periodically monitor leukocyte count. (5.8)
- Phlebitis: To reduce the risk of local irritation and phlebitis administer Vancomycin Injection by a secure intravenous route of administration. (5.9)
- Development of Drug-Resistant Bacteria: Prescribing Vancomycin Injection in the absence of a proven or strongly suspected bacterial infection is unlikely to provide benefit to the patient and increases the risk of the development of drug resistant bacteria. (5.10)

6 ADVERSE REACTIONS

The common adverse reactions are anaphylaxis, "red man syndrome", acute kidney injury, hearing loss, neutropenia. (6.1)

To report SUSPECTED ADVERSE REACTIONS, contact Xellia Pharmaceuticals USA, LLC at 1-833-295-6953 or FDA at 1-800-FDA-1088 or www.fda.gov/medwatch.

7 DRUG INTERACTIONS

- Anesthetic Agents: Concomitant administration of vancomycin and anesthetic agents has been associated with erythema and histamine-like flushing. (2.1, 7.1)
- Piperacillin/Tazobactam: Increased incidence of acute kidney injury in patients receiving concomitant piperacillin/tazobactam and vancomycin as compared to vancomycin alone. Monitor kidney function in patients. (7.2)

FULL PRESCRIBING INFORMATION

WARNING: POTENTIAL RISK OF EXPOSURE TO EXCIPIENTS DURING THE FIRST OR SECOND TRIMESTER OF PREGNANCY

If use of vancomycin is needed during the first or second trimester of pregnancy, use other available formulations of vancomycin. This formulation of vancomycin injection contains the excipients polyethylene glycol (PEG 400) and N-acetyl D-alanine (NADA), which resulted in fetal malformations in animal reproduction studies at dose exposures approximately 8 and 32 times, respectively, higher than the exposures at the human equivalent dose [see Warnings and Precautions (5.1) and Use in Specific Populations (8.1)].

1 INDICATIONS AND USAGE

1.1 Septicemia

Vancomycin Injection is indicated in adults and pediatric patients (1 month and older) for the treatment of septicemia due to:

- Susceptible isolates of methicillin-resistant Staphylococcus aureus (MRSA) and coagulase negative staphylococci.
- Methicillin-susceptible staphylococci in penicillin-allergic patients, or those patients who cannot receive or who have failed to respond to other drugs, including penicillins or cephalosporins.

1.2 Infective Endocarditis

Vancomycin Injection is indicated in adults and pediatric patients (1 month and older) for the treatment of infective endocarditis due to:

- Susceptible isolates of MRSA.
- Viridans group streptococci Streptococcus gallolyticus (previously known as Streptococcus bovis), Enterococcus species and Corynebacterium species. For enterococcal endocarditis, use Vancomycin Injection in combination with an aminoglycoside.
- Methicillin-susceptible staphylococci in penicillin-allergic patients, or those patients who cannot receive or who have failed to respond to other drugs, including penicillins or cephalosporins.

Vancomycin Injection is indicated in adults and pediatric patients (1 month and older) for the treatment of early-onset prosthetic valve endocarditis caused by Staphylococcus epidermidis in combination with rifampin and an aminoglycoside.

1.3 Skin and Skin Structure Infections

Vancomycin Injection is indicated in adults and pediatric patients (1 month and older) for the treatment of skin and skin structure infections due to:

- Susceptible isolates of MRSA and coagulase negative staphylococci.
- Methicillin-susceptible staphylococci in penicillin-allergic patients, or those patients who cannot receive or who have failed to respond to other drugs, including penicillins or cephalosporins.

1.4 Bone Infections

Vancomycin Injection is indicated in adults and pediatric patients (1 month and older) for the treatment of bone infections due to:

- Susceptible isolates of MRSA and coagulase negative staphylococci.
- Methicillin-susceptible staphylococci in penicillin-allergic patients, or those patients who cannot receive or who have failed to respond to other drugs, including penicillins or cephalosporins.

1.5 Lower Respiratory Tract Infections

Vancomycin Injection is indicated in adults and pediatric patients (1 month and older) for the treatment of lower respiratory tract infections due to:

- Susceptible isolates of MRSA
- Methicillin-susceptible staphylococci in penicillin-allergic patients, or those patients who cannot receive or who have failed to respond to other drugs, including penicillins or cephalosporins.

1.6 Usage

To reduce the development of drug-resistant bacteria and maintain the effectiveness of Vancomycin Injection and other antibacterial drugs, Vancomycin Injection should be used only to treat or prevent infections that are proven or strongly suspected to be caused by susceptible bacteria. When culture and susceptibility information are available, they should be considered in selecting or modifying antibacterial therapy. In the absence of such data, local epidemiology and susceptibility patterns may contribute to the empiric selection of therapy.

2 DOSAGE AND ADMINISTRATION

2.1 Important Administration Instructions

- Obtain a pregnancy test in females of reproductive potential prior to initiating treatment with Vancomycin Injection [see Warnings and Precautions (5.1), and Use in Specific Populations (8.1, 8.3)].
- Use this formulation of Vancomycin Injection only in patients who require the entire (500 mg, 750 mg, 1 g, 1.25 g, 1.5 g, 1.75 g or 2 g) dose and not any fraction thereof.
- Vancomycin Injection in transparent single-dose flexible bags are intended for intravenous use only. Do NOT administer orally.
- To reduce the risk of infusion related adverse reactions, administer Vancomycin Injection by intravenous infusion over 60 minutes or greater [see Warnings and Precautions (5.2) and Adverse Reactions (6.1)]. An infusion rate of 10 mg/min or less is associated with fewer infusion-related events [see Warnings and Precautions (5.2)]. Infusion related events may occur, however, at any rate or concentration.
- Drug additives should not be made to this solution.
- Vancomycin Injection concentrations of no more than 5 mg/mL are recommended in adults [see Dosage and Administration (2.2)]. See also age-specific recommendations [see Dosage and Administration (2.3)].
- Administer Vancomycin Injection prior to intravenous anesthetic agents to reduce the risk of infusion related adverse reactions [see Warnings and Precautions (5.2)].
- Administer Vancomycin Injection by a secure intravenous route of administration to avoid local irritation and phlebitis reactions [see Warnings and Precautions (5.9)].

2.2 Dosage in Adult Patients with Normal Renal Function

The usual daily intravenous dose is 2 g divided either as 500 mg every 6 hours or 1 g every 12 hours. Administer each dose by intravenous infusion over a period of 60 minutes or greater. Other patient factors, such as age or obesity, may call for modification of the usual intravenous daily dose. The initial daily dose should be no less than 15 mg/kg.

2.3 Dosage in Pediatric Patients (1 Month and Older) with Normal Renal Function

Use this formulation of Vancomycin Injection only in pediatric patients (1 month and older) who require the entire dose (500 mg, 750 mg, 1 g, 1.25 g, 1.5 g, 1.75 g or 2 g) of this single-dose flexible bag and not any fraction of it [see Dosage Forms and Strengths (3)].

The usual intravenous dosage of vancomycin is 10 mg/kg per dose given every 6 hours. Each dose should be administered over a period of at least 60 minutes. Close monitoring of serum concentrations of vancomycin may be warranted in these patients.

2.4 Dosage in Patients with Renal Impairment

Dosage adjustment must be made in patients with renal impairment. The initial dose should be no less than 15 mg/kg in patients with any degree of renal impairment.

In the elderly, greater dosage reductions than expected may be necessary because of decreased renal function. Measure trough vancomycin serum concentrations to guide therapy, especially in seriously ill patients with changing renal function.

For functionally anephric patients, an initial dose of 15 mg/kg of body weight should be given to achieve prompt therapeutic serum concentration. A dose of 1.9 mg/kg/24 h should be given after the initial dose of 15 mg/kg.

2.5 Directions for Use of Vancomycin Injection and Storage Instructions

Vancomycin Injection in transparent single-dose flexible bag is for intravenous administration only.

Vancomycin Injection is room temperature stable, ready-to-use drug product.

Preparation for Intravenous Administration:

1. Remove the flexible bag from aluminum overpouch.
2. Check for minute leaks by squeezing the bag firmly. If leaks are detected, discard solution because sterility may be impaired. Leaks may be more readily detected by wrapping the bag with blotting paper or a tissue before squeezing.
3. Do not add supplemental medication.
4. Visually inspect the flexible bag. If the outlet port protector is damaged, detached, or not present, discard the flexible bag as solution path sterility may be impaired. If after visual inspection the solution is cloudy or if an insoluble precipitate is noted or if any seals are not intact, the flexible bag should be discarded.
5. The solution in the flexible bag remains chemically stable for 28 days at room temperature (up to 25°C/77°F) after removal from the aluminum overpouch. Discard unused drug.
6. Suspend the flexible bag from eyelet support.
7. Remove protector from outlet port at bottom of flexible bag.
8. Attach administration set. Refer to complete directions accompanying set.
9. Use sterile equipment.

Do NOT use flexible bags in series connections. Such use could result in an embolism due to residual air being drawn from the primary container before administration of the fluid from the secondary container is complete.

2.6 Incompatibilities for Intravenous Use

Vancomycin solution has a low pH and may cause chemical or physical instability when it is mixed with other compounds.

Mixtures of solutions of vancomycin and beta-lactam antibacterial drugs have been shown to be physically incompatible. The likelihood of precipitation increases with higher concentrations of vancomycin. It is recommended to adequately flush the intravenous lines between the administration of these antibacterial drugs.

3 DOSAGE FORMS AND STRENGTHS

Vancomycin Injection, USP is a ready to use clear, colorless to light brown solution in single-dose flexible bags containing 500 mg vancomycin in 100 mL, 750 mg vancomycin in 150 mL, 1 g vancomycin in 200 mL, 1.25 g vancomycin in 250 mL, 1.5 g vancomycin in 300 mL, 1.75 g vancomycin in 350 mL and 2 g vancomycin in 400 mL of liquid [see Description (11)]. The flexible bags are supplied in sealed aluminum overpouches.

4 CONTRAINDICATIONS

Vancomycin Injection is contraindicated in patients with known hypersensitivity to vancomycin.

5 WARNINGS AND PRECAUTIONS

5.1 Potential Risk of Exposure to Excipients During the First or Second Trimester of Pregnancy

If use of vancomycin is needed during the first or second trimester of pregnancy, use other available formulations of vancomycin. This formulation of Vancomycin Injection contains the excipients polyethylene glycol (PEG 400) and N-acetyl D-alanine (NADA). In a rabbit reproduction study, fetal spinal malformations occurred when the excipient PEG 400 was administered at dose exposures approximately 8 times the exposure at the maximum daily human dose. In a separate rabbit reproduction study, fetal spinal and cardiovascular malformations occurred when the excipient NADA was administered at dose exposures approximately 32 times the exposure at the maximum daily human dose. The active ingredient vancomycin is not known to be associated with embryo-fetal toxicity [see Use in Specific Populations (8.1)].

5.2 Infusion Reactions

Hypotension, including shock and cardiac arrest, wheezing, dyspnea, urticaria, muscular and chest pain may occur with rapid Vancomycin Injection administration. The reactions may be more severe in younger patients, particularly children, and in patients receiving concomitant muscle relaxant anesthetics.

Rapid intravenous administration of Vancomycin Injection may also be associated with "red man syndrome", which manifests as pruritus and erythema that involves the face, neck and upper torso.

Infusion-related adverse reactions are related to both the concentration and the rate of administration of vancomycin. Infusion-related adverse reactions may occur, however, at any rate or concentration.

Administer Vancomycin Injection over a period of 60 minutes or greater to reduce the risk of infusion-related adverse reactions. In selected patients in need of fluid restriction, a concentration up to 10 mg/mL may be used; use of such higher concentrations may increase the risk of infusion-related adverse reactions. Administer prior to intravenous anesthetic agents when feasible. Stop the infusion if a reaction occurs.

5.3 Nephrotoxicity

Vancomycin Injection can result in acute kidney injury (AKI), including acute renal failure, mainly due to interstitial nephritis or less commonly acute tubular necrosis. AKI is manifested by increasing blood urea nitrogen (BUN) and serum creatinine (Cr). The risk of AKI increases with higher vancomycin serum levels, prolonged exposure, concomitant administration of other nephrotoxic drugs, concomitant administration of piperacillin-tazobactam [see Drug Interactions (7.2)], volume depletion, pre-existing renal impairment and in critically ill patients and patients with co-morbid conditions that predispose to renal impairment.

Monitor serum vancomycin concentrations and renal function in all patients receiving Vancomycin Injection. More frequent monitoring is recommended in patients with comorbidities that predispose to impairment in renal function or are concomitantly receiving other nephrotoxic drugs, in critically ill patients, in patients with changing renal function, and in patients requiring higher therapeutic vancomycin levels. If acute kidney injury occurs, discontinue Vancomycin Injection or reduce the dose.

5.4 Ototoxicity

Ototoxicity has occurred in patients receiving vancomycin. It may be transient or permanent. Ototoxicity manifests as tinnitus, hearing loss, dizziness or vertigo. The risk is higher in older patients, patients who are receiving higher doses, who have an underlying hearing loss, who are receiving concomitant therapy with another ototoxic agent, such as an aminoglycoside or who have underlying renal impairment. Monitor for signs and symptoms of ototoxicity during therapy. Monitor serum vancomycin concentrations and renal function in all patients receiving parenteral vancomycin. Discontinue Vancomycin Injection if ototoxicity occurs. Dosage of Vancomycin Injection must be adjusted for patients with renal impairment [see Dosage and Administration (2.3)]. Serial tests of auditory function may be helpful in order to minimize the risk of ototoxicity.

5.5 Severe Dermatologic Reactions

Severe dermatologic reactions such as toxic epidermal necrolysis (TEN), Stevens-Johnson syndrome (SJS), drug reaction with eosinophilia and systemic symptoms (DRESS), acute generalized exanthematous pustulosis (AGEP), and linear IgA bullous dermatosis (LABD) have been reported in association with the use of vancomycin. Cutaneous signs or symptoms reported include skin rashes, mucosal lesions, and blisters.

Discontinue Vancomycin Injection at the first appearance of signs and symptoms of TEN, SJS, DRESS, AGEP, or LABD.

5.6 Clostridioides Difficile-Associated Diarrhea (CDAD)

Clostridioides difficile-associated diarrhea (CDAD) has been reported with use of nearly all antibacterial agents, including vancomycin and may range in severity from mild diarrhea to fatal colitis. Treatment with antibacterial agents alters the normal flora of the colon leading to overgrowth of C. difficile.

C. difficile produces toxins A and B which contribute to the development of CDAD. Hypertoxin producing strains of C. difficile cause increased morbidity and mortality, as these infections can be refractory to antimicrobial therapy and may require colectomy. CDAD must be considered in all patients who present with diarrhea following antibacterial use. Careful medical history is necessary since CDAD has been reported to occur over two months after the administration of antibacterial agents.

If CDAD is suspected or confirmed, ongoing antibacterial use not directed against C. difficile may need to be discontinued. Appropriate fluid and electrolyte management, protein supplementation, antibacterial treatment of C. difficile, and surgical evaluation should be instituted as clinically indicated.

Clinically significant serum concentrations have been reported in some patients being treated for active C. difficile-induced pseudomembranous colitis after multiple oral doses of vancomycin.

Prolonged use of Vancomycin Injection may result in the overgrowth of nonsusceptible microorganisms. Careful observation of the patient is essential. If superinfection occurs during therapy, appropriate measures should be taken. In rare instances, there have been reports of pseudomembranous colitis due to C. difficile developing in patients who received intravenous vancomycin.

5.7 Hemorrhagic Occlusive Retinal Vasculitis (HORV)

Hemorrhagic occlusive retinal vasculitis, including permanent loss of vision, occurred in patients receiving intracameral or intravitreal administration of vancomycin during or after cataract surgery. The safety and efficacy of vancomycin administered by the intracameral or the intravitreal route have not been established by adequate and well-controlled trials. Vancomycin is not indicated for the prophylaxis of endophthalmitis.

5.8 Neutropenia

Reversible neutropenia has been reported in patients receiving vancomycin [see Adverse Reactions (6.1)]. Patients who will undergo prolonged therapy with vancomycin or those who are receiving concomitant drugs which may cause neutropenia should have periodic monitoring of the leukocyte count.

5.9 Phlebitis and Other Administration Site Reactions

Inflammation at the site of injection of vancomycin has been reported. Vancomycin is irritating to tissue and must be given by a secure intravenous route of administration to reduce the risk of local irritation and phlebitis.

Administration of vancomycin by intramuscular (IM), intraperitoneal, intrathecal (intralumbar or intraventricular), or intravitreal routes has not been approved and is not recommended. The safety and efficacy of vancomycin administered by the intrathecal (intralumbar or intraventricular) route or by the intraperitoneal route have not been established by adequate and well controlled trials.

Pain, tenderness, and necrosis occur with IM injection of vancomycin or with inadvertent extravasation. Thrombophlebitis may occur, the frequency and severity of which can be minimized by slow infusion of the drug and by rotation of venous access sites.

Intraperitoneal administration during continuous ambulatory peritoneal dialysis (CAPD) can result in chemical peritonitis. Manifestations range from cloudy dialysate alone to a cloudy dialysate accompanied by variable degrees of abdominal pain and fever. This syndrome appears to be resolved after discontinuation of intraperitoneal vancomycin.

About 60% of an intraperitoneal dose of vancomycin administered during peritoneal dialysis is absorbed systemically in 6 hours. Serum concentrations of about 10 mcg/mL are achieved by intraperitoneal injection of 30 mg/kg of vancomycin. However, the safety and efficacy of the intraperitoneal use of vancomycin has not been established in adequate and well-controlled trials.

5.10 Development of Drug-Resistant Bacteria

Prescribing Vancomycin Injection in the absence of a proven or strongly suspected bacterial infection or a prophylactic indication is unlikely to provide benefit to the patient and increases the risk of the development of drug-resistant bacteria.

6 ADVERSE REACTIONS

The following clinically significant adverse reactions are described elsewhere in the labeling:

- Infusion Reactions [see Warnings and Precautions (5.2)]
- Nephrotoxicity [see Warnings and Precautions (5.3)]
- Ototoxicity [see Warnings and Precautions (5.4)]
- Severe Dermatologic Reactions [see Warnings and Precautions (5.5)]
- Clostridioides difficile-Associated Diarrhea [see Warnings and Precautions (5.6)]
- Hemorrhagic Occlusive Retinal Vasculitis [see Warnings and Precautions (5.7)]
- Neutropenia [see Warnings and Precautions (5.8)]

6.1 Clinical Trials Experience

Because clinical trials are conducted under widely varying conditions, adverse reaction rates observed in the clinical trials of a drug cannot be directly compared to rates in the clinical trials of another drug and may not reflect the rates observed in practice.

The following adverse reactions associated with the use of vancomycin were identified in clinical trials:

Immune System Disorders: Hypersensitivity reactions including anaphylaxis and "red man syndrome"[see Warnings and Precautions (5.2)]

Skin and Subcutaneous Tissue Disorders: Erythema (especially of the face, neck and upper torso) and pruritus which are manifestations of rashes including exfoliative dermatitis. Toxic epidermal necrolysis (TEN), Stevens-Johnson syndrome (SJS), Linear IgA bullous dermatosis (LABD) [see Warnings and Precautions (5.5)].

Renal and Urinary Disorders: Acute kidney injury and interstitial nephritis

Ear and Labyrinth Disorders: Tinnitus, hearing loss, vertigo

Blood and Lymphatic System Disorders: Agranulocytosis, neutropenia, pancytopenia, leukopenia, thrombocytopenia, eosinophilia

Gastrointestinal Disorders: Pseudomembranous colitis [see Warnings and Precautions (5.6)]

Cardiac Disorders: Cardiac arrest, chest pain

General Disorders and Administration Site Conditions: General discomfort, fever, chills, phlebitis, injection site irritation, injection site pain and necrosis following intramuscular injection, chemical peritonitis following intraperitoneal administration (Vancomycin Injection is not approved for intramuscular and intraperitoneal administration) [see Warnings and Precautions (5.9)]

Laboratory Abnormalities: Elevated blood urea nitrogen, elevated serum creatinine

Musculoskeletal and Connective Tissue Disorders: Muscle pain

Nervous System Disorders: Dizziness

Respiratory, Thoracic and Mediastinal Disorders: Wheezing, dyspnea

Vascular Disorders: Hypotension, shock, vasculitis

6.2 Post Marketing Experience

The following adverse reactions have been identified during postmarketing use of vancomycin. Because these reactions are reported voluntarily from a population of uncertain size, it is not possible to reliably estimate their frequency or establish a causal relationship to drug exposure.

Skin and Subcutaneous Tissue Disorders: Drug reaction with eosinophilia and systemic symptoms (DRESS), acute generalized exanthematous pustulosis (AGEP) [see Warnings and Precautions (5.5)].

7 DRUG INTERACTIONS

7.1 Anesthetic Agents

Concomitant administration of vancomycin and anesthetic agents has been associated with erythema and histamine-like flushing [see Warnings and Precautions (5.2) and Use in Specific Populations (8.4)].

7.2 Piperacillin-Tazobactam

Studies have detected an increased incidence of acute kidney injury in patients administered concomitant piperacillin/tazobactam and vancomycin as compared to vancomycin alone. Monitor kidney function in patients receiving concomitant piperacillin/tazobactam and vancomycin. No pharmacokinetic interactions have been noted between piperacillin/tazobactam and vancomycin.

7.3 Ototoxic and/or Nephrotoxic Drugs

Concurrent and/or sequential systemic or topical use of other potentially neurotoxic and/or nephrotoxic drugs requires more frequent monitoring of renal function.

8 USE IN SPECIFIC POPULATIONS

8.1 Pregnancy

Risk Summary

This formulation of Vancomycin Injection is not recommended for use during the first or second trimester of pregnancy because it contains the excipients, PEG 400 and NADA, which caused fetal malformations in animal reproduction studies (see Data). Advise pregnant women of the potential risk to the fetus. If therapy with Vancomycin Injection is needed during the first or second trimester of pregnancy, use other available formulations of vancomycin, free of PEG 400 and NADA.

The available data on use of this formulation of Vancomycin Injection (with the excipients PEG 400 and NADA) in pregnant women are insufficient to evaluate for a drug-associated risk of major birth defects, miscarriage, or other adverse maternal or fetal outcomes. Available published data on vancomycin (without the excipients PEG 400 and NADA) use in pregnancy during the second and third trimesters have not shown an association with adverse pregnancy related outcomes (see Data). There are no available data on first trimester use of vancomycin in pregnant women to assess the risk of major birth defects or miscarriage. Vancomycin alone did not show adverse developmental effects when administered intravenously to pregnant rats and rabbits during organogenesis at doses less than or equal to the recommended maximum human dose based on body surface area (see Data).

Reproduction studies in rabbits with intravenous doses of PEG 400 at approximately 8 times the maximum daily human dose based on systemic exposures of PEG 400 during organogenesis resulted in fetal spinal malformations. Reproduction studies in rabbits and rats using intravenous doses of NADA at approximately 32 and 20 times the maximum daily human dose, respectively, based on systemic exposures of NADA resulted in maternal toxicity and fetal spinal and cardiovascular malformations in rabbits, and maternal toxicity with no adverse embryo-fetal effects in rats. Vancomycin alone did not show adverse developmental effects when administered intravenously to pregnant rats and rabbits during organogenesis at doses less than or equal to the recommended maximum human dose based on body surface area (see Data).

All pregnancies have a background risk of birth defect, loss, or other adverse outcomes. In the U.S. general population, the estimated background risk of major birth defects and miscarriage in clinically recognized pregnancies is 2 to 4% and 15 to 20%, respectively.

Data

Human Data

Available data from postmarketing cases on use of this formulation of vancomycin injection (with the excipients PEG 400 and NADA) in pregnant women are insufficient to evaluate for a drug-associated risk of major birth defects, miscarriage, or other adverse maternal or infant outcomes.

There are no available data on first trimester use of vancomycin (without the excipients PEG 400 and NADA); however, available published data on use in pregnancy during the second and third trimesters have not shown an association with adverse pregnancy related outcomes.

A published study evaluated hearing loss and nephrotoxicity in infants of 10 pregnant intravenous drug users treated with vancomycin (formulation did not include the excipients PEG 400 and NADA) for suspected or documented methicillin-resistant Staphylococcus aureus in the second or third trimester.

The comparison groups were 10 uninfected non-intravenous drug-dependent patients, and 10 uninfected intravenous drug-dependent patients who served as substance abuse controls. No infant in the vancomycin exposed group had abnormal sensorineural hearing at 3 months of age or nephrotoxicity.

A published prospective study assessed outcomes in 55 pregnant women with a positive Group B streptococcus (GBS) culture and a high-risk penicillin allergy with resistance to clindamycin or unknown sensitivity who were administered vancomycin (formulation did not include the excipients PEG 400 and NADA) at the time of delivery. Vancomycin dosing ranged from the standard 1 g intravenously every 12 hours to 20 mg/kg intravenous every 8 hours (maximum individual dose 2 g). No major adverse reactions were recorded either in the mothers or their newborns. None of the newborns had sensorineural hearing loss. Neonatal renal function was not examined, but all of the newborns were discharged in good condition.

Animal Data

Vancomycin did not cause fetal malformations when administered during organogenesis to pregnant rats (gestation days 6 to 15) and rabbits (gestation days 6 to 18) at the equivalent recommended maximum human dose (based on body surface area comparisons) of 200 mg/kg/day IV to rats or 120 mg/kg/day IV to rabbits. No effects on fetal weight or development were seen in rats at the highest dose tested or in rabbits given 80 mg/kg/day (approximately 1 and 0.8 times the recommended maximum human dose based on body surface area, respectively). Maternal toxicity was observed in rats (at doses 120 mg/kg and above) and rabbits (at 80 mg/kg and above).

Animal reproduction studies conducted in rabbits administered intravenous PEG 400 at 2000 mg/kg (approximately 8 times the maximum daily human dose, based on AUC levels of PEG 400) during organogenesis (gestation days 6 to 19) resulted in fetal scoliosis (thoracic and lumbar) and increased incidence of delayed or incomplete ossification of the pubes, epiphyses, and talus bones. No maternal toxicity was observed up to the maximum dose tested.

Similarly, in animal reproduction studies conducted in pregnant rabbits (gestation days 6 to 19) and pregnant rats (gestation days 6 to 17) administered intravenous NADA at 1680 and 3780 mg/kg, respectively (at 32 times or greater based on AUC levels of NADA) resulted in fetal scoliosis and a spectrum of cardiovascular anomalies in rabbits and no adverse effects on fetuses in rats. Increased incidence of delayed or incomplete ossifications of the metacarpals/metatarsals/phalanges and increased ossification (fused jugal/maxilla bones) were observed in rabbits at 1680 mg/kg. Minor non adverse fetal skeletal abnormalities were observed in rats at 3780 mg/kg which was also associated with maternal toxicity including increased incidence of litter loss [see Clinical Pharmacology (12.3)].

No animal studies have been conducted to evaluate the potential reproductive and embryo-fetal effects of Vancomycin Injection (with the excipients PEG 400 and NADA).

8.2 Lactation

Risk Summary

There are insufficient data to inform the levels of vancomycin in human milk. There are no data on the effects of vancomycin on the breastfed infant or milk production. The developmental and health benefits of breastfeeding should be considered along with the mother's clinical need for Vancomycin Injection and any potential adverse effects on the breastfed infant from Vancomycin Injection or from the underlying maternal condition.

8.3 Females and Males of Reproductive Potential

Pregnancy Testing

Perform a pregnancy test in females of reproductive potential prior to prescribing this formulation of vancomycin [see Warnings and Precautions (5.1) and Use in Specific Populations (8.1)].

8.4 Pediatric Use

Vancomycin Injection is indicated in pediatric patients (1 month and older) [see Indications and Usage (1.1 to 1.5) and Dosage and Administration (2.2)]. In pediatric patients, monitor vancomycin serum concentration and renal function when administering Vancomycin Injection [see Dosage and Administration (2.2, 2.3) and Warnings and Precautions (5.2)]. More severe infusion related reactions related to vancomycin administration may occur in pediatric patients. Concomitant administration of vancomycin and intravenous anesthetic agents has been associated with erythema and histamine-like flushing in all patients including pediatric patients [see Warnings and Precautions (5.2)].

8.5 Geriatric Use

Vancomycin is known to be substantially excreted by the kidney, and the risk of adverse reactions to this drug may be greater in patients with impaired renal function. Because elderly patients are more likely to have decreased renal function, care should be taken in dose selection [see Dosage and Administration (2.2)], and it may be useful to monitor renal function [see Warnings and Precautions (5.2)].

10 OVERDOSAGE

Supportive care is advised, with maintenance of glomerular filtration. Vancomycin is poorly removed by dialysis. Hemofiltration and hemoperfusion with polysulfone resin have been reported to result in increased vancomycin clearance.

For current information on the management of overdosage, contact the National Poison Control Center at 1-800-222-1222 or www.poison.org.

11 DESCRIPTION

Vancomycin Injection, USP, in single-dose flexible bags contain vancomycin as vancomycin hydrochloride. It is a tricyclic glycopeptide antibacterial drug derived from Amycolatopsis orientalis (formerly Nocardia orientalis). The molecular formula is C66H75Cl2N9O24∙HCl and the molecular weight is 1,485.71. The chemical name is (Sa)-(3S,6R,7R,22R,23S,26S,36R,38aR)-44-{[2-O-(3-amino-2,3,6-trideoxy-3-C-methyl-α-L-lyxo-hexopyranosyl)-β-D-glucopyranosyl]-oxy}-3-(carbamoylmethyl)-10,19-dichloro-2,3,4,5,6,7,23,24,25,26,36,37,38,38a-tetradecahydro-7,22,28,30,32-pentahydroxy-6-[(2R)-4-methyl-2-(methylamino]valeramido]-2,5,24,38,39-pentaoxo-22H-8,11:18,21-dietheno-23,36(iminometha-no)-13,16:31,35-dimetheno-1H,16H-[1,6,9]-oxadiazacyclohexadecino-[4,5-m][10,2,16]-benzoxa-diazacyclotetracosine-26-carboxylic acid, monohydrochloride. Vancomycin hydrochloride has the following structural formula:

Vancomycin Injection, USP, in single-dose flexible bags are sterile, nonpyrogenic premixed 100 mL, 150 mL, 200 mL, 250 mL, 300 mL, 350 mL or 400 mL solution containing 500 mg, 750 mg, 1 g, 1.25 g, 1.5 g, 1.75 g or 2 g vancomycin, respectively, as vancomycin hydrochloride. Each 100 mL of solution contains 1.8 mL polyethylene glycol 400, 1.36 g N-acetyl-D-alanine, 1.26 g L-lysine hydrochloride (monochloride) in water for injection. Hydrochloric acid and sodium hydroxide are used for pH adjustment. The pH is 4.5 to 5.5 and the osmolarity is 350 to 475 mOsmol/L.

12 CLINICAL PHARMACOLOGY

12.1 Mechanism of Action

Vancomycin is an antibacterial drug [see Microbiology (12.4)].

12.2 Pharmacodynamics

The pharmacodynamics of vancomycin is unknown.

12.3 Pharmacokinetics

In subjects with normal kidney function, multiple intravenous dosing of 1 g of vancomycin (15 mg/kg) infused over 60 minutes produces mean plasma concentrations of approximately 63 mcg/mL immediately after the completion of infusion, mean plasma concentrations of approximately 23 mcg/mL 2 hours after infusion, and mean plasma concentrations of approximately 8 mcg/mL 11 hours after the end of the infusion. Multiple dosing of 500 mg infused over 30 minutes produces mean plasma concentrations of about 49 mcg/mL at the completion of infusion, mean plasma concentrations of about 19 mcg/mL 2 hours after infusion, and mean plasma concentrations of about 10 mcg/mL 6 hours after infusion. The plasma concentrations during multiple dosing are like those after a single dose.

In healthy subjects administered a single 1g dose of Vancomycin Injection, geometric mean (geometric %CV) AUC0-inf values for NADA, PEG 400, and vancomycin were 209 (19.6%), 405 (12.5%), and 219 (13.7%) mcg*h/mL, respectively. Based on a population pharmacokinetic analysis, 1g Vancomycin Injection administered over 1.5 hours every 12 hours achieves a geometric mean (95% prediction interval) steady state AUC0-24 exposure of 384 (277-547) , 734 (550-994), and 384 (261-567) mcg*h/mL for NADA, PEG 400, and vancomycin in healthy subjects, respectively.

Distribution

The volume of distribution ranges from 0.3 to 0.43 L/kg after intravenous administration.

Vancomycin is approximately 55% serum protein bound as measured by ultrafiltration at vancomycin serum concentrations of 10 to 100 mcg/mL. After intravenous administration of vancomycin, inhibitory concentrations are present in pleural, pericardial, ascitic, and synovial fluids; in urine; in peritoneal dialysis fluid; and in atrial appendage tissue. Vancomycin does not readily diffuse across normal meninges into the spinal fluid; but, when the meninges are inflamed, penetration into the spinal fluid occurs.

Elimination

Mean plasma clearance is about 0.058 L/kg/h, and mean renal clearance is about 0.048 L/kg/h. The mean elimination half-life of vancomycin from plasma is 4 to 6 hours in subjects with normal renal function. In anephric patients, the mean elimination half-life is 7.5 days. Total body and renal clearance of vancomycin may be reduced in the elderly.

Metabolism

There is no apparent metabolism of the vancomycin.

Excretion

In the first 24 hours after intravenous administration, about 75% of an administered dose of vancomycin is excreted in urine by glomerular filtration. Renal impairment slows excretion of vancomycin.

In the first 48 hours after intravenous administration of a single 1 g dose of Vancomycin Injection, the percent excreted unchanged in urine was approximately 80% and 50% for NADA and PEG 400, respectively.

12.4 Microbiology

Mechanism of Action

The bactericidal action of vancomycin results primarily from inhibition of cell-wall biosynthesis. In addition, vancomycin alters bacterial-cell-membrane permeability and RNA synthesis.

Resistance

Vancomycin is not active in vitro against gram-negative bacilli, mycobacteria, or fungi. There is no cross-resistance between vancomycin and other antibacterials.

Interaction with Other Antimicrobials

The combination of vancomycin and an aminoglycoside acts synergistically in vitro against many isolates of Staphylococcus aureus, Streptococcus gallolyticus (previously known as Streptococcus bovis), Enterococcus spp, and the viridans group streptococci.

Antimicrobial Activity

Vancomycin has been shown to be active against most isolates of the following bacteria, both in vitro and in clinical infections [see Indications and Usage (1)].

Aerobic Gram-Positive Bacteria

Corynebacterium spp.

Enterococcus spp. (including Enterococcus faecalis)

Staphylococcus aureus (including methicillin-resistant and methicillin-susceptible isolates)

Coagulase negative staphylococci (including S.epidermidis and methicillin-resistant isolates)

Streptococcus gallolyticus (previously known as Streptococcus bovis)

Viridans group streptococci

The following in vitro data are available, but their clinical significance is unknown.

At least 90 percent of the following bacteria exhibit an in vitro minimum inhibitory concentration (MIC) less than or equal to the susceptible breakpoint for vancomycin against isolates of similar genus or organism group. However, the efficacy of vancomycin in treating clinical infections caused by these bacteria has not been established in adequate and well-controlled clinical trials.

Aerobic Gram-Positive Bacteria

Listeria monocytogenes

Streptococcus pyogenes

Streptococcus pneumoniae

Streptococcus agalactiae

Anaerobic Gram-Positive Bacteria

Actinomyces species

Lactobacillus species

Susceptibility Testing

For specific information regarding susceptibility test interpretive criteria and associated test methods and quality control standards recognized by FDA for this drug, please see: https://www.fda.gov/STIC.

13 NONCLINICAL TOXICOLOGY

13.1 Carcinogenesis, Mutagenesis, Impairment of Fertility

Although no long-term studies in animals have been performed to evaluate carcinogenic potential, no mutagenic potential of vancomycin was found in standard laboratory tests. No definitive fertility studies have been performed.

13.2 Animal Toxicology and/or Pharmacology

In animal studies, hypotension and bradycardia occurred in dogs receiving an intravenous infusion of vancomycin 25 mg/kg, at a concentration of 25 mg/mL and an infusion rate of 13.3 mL/min.

15 REFERENCES

1. Byrd RA., Gries CL, Buening M.: Developmental Toxicology Studies of Vancomycin Hydrochloride Administered Intravenously to Rats and Rabbits. Fundam Appl Toxicol 1994; 23: 590-597.

16 HOW SUPPLIED/STORAGE AND HANDLING

16.1 How Supplied

Vancomycin Injection, USP is supplied as a ready to use clear, colorless to light brown solution in single-dose flexible bags containing 500 mg, 750 mg, 1 g, 1.25 g, 1.5 g, 1.75 g and 2 g vancomycin in 100 mL, 150 mL, 200 mL, 250 mL, 300 mL, 350 mL and 400 mL of liquid (consists of water and PEG together with the excipients NADA and lysine) [see Description (11)]. The flexible bags are supplied in sealed aluminum overpouches. The bags are supplied in the following packages:

16.2 Storage

NDC number | Packaging configuration
70594-041-02 | Carton of six 500 mg/100 mL bags
70594-041-03 | Carton of twelve 500 mg/100 mL bags
70594-056-02 | Carton of six 750 mg/150 mL bags
70594-056-03 | Carton of twelve 750 mg/150 mL bags
70594-042-02 | Carton of six 1 g/200 mL bags
70594-042-03 | Carton of twelve 1 g/200 mL bags
70594-057-02 | Carton of six 1.25 g/250 mL bags
70594-043-02 | Carton of six 1.5 g/300 mL bags
70594-058-02 | Carton of six 1.75 g/350 mL bags
70594-044-02 | Carton of six 2 g/400 mL bags

Store below 25°C (77ºF), in original package. Product should be used within 28 days of removal from aluminum overpouch.

17 PATIENT COUNSELING INFORMATION

Potential Risk of Exposure to Excipients During the First or Second Trimester of Pregnancy

Advise patients to notify their healthcare provider if they are pregnant prior to treatment with this formulation of vancomycin [see Boxed Warning, Warnings and Precautions (5.1) and Use in Specific Populations (8.1)].

Infusion Reactions During or After Intravenous Use

Advise patients that generalized skin redness, skin rash, itching, flushing, muscle pain, chest pain, shortness of breath, wheezing, or dizziness may occur during Vancomycin Injection infusion. These reactions can be lessened or prevented by infusing the drug over at least 60 minutes [see Warnings and Precautions (5.2)].

Acute Kidney Injury

Advise patients that Vancomycin Injection can result in kidney damage and that blood tests are required to monitor vancomycin blood levels and kidney function during therapy [see Warnings and Precautions (5.3)].

Hearing Loss or Balance Problems

Advise patients that Vancomycin Injection may result in decreased hearing and to report hearing loss or balance problems to their health care provider [see Warnings and Precautions (5.4)].

Severe Dermatologic Reactions

Advise patients about the signs and symptoms of serious skin manifestations. Instruct patients to stop Vancomycin Injection immediately and promptly report the first signs or symptoms of skin rash, mucosal lesions or blisters to their healthcare provider [see Warnings and Precautions (5.5)].

Diarrhea

Diarrhea is a common problem caused by antibacterial drugs, including vancomycin, which usually ends when the antibacterial drug is discontinued. Sometimes after starting treatment with antibacterial drugs, patients can develop watery and bloody stools (with or without stomach cramps and fever) even as late as two or more months after having taken the last dose of the antibacterial drug. If this occurs, patients should contact their physician as soon as possible [see Warnings and Precautions (5.2)].

Antibacterial Resistance

Patients should be counseled that antibacterial drugs including vancomycin, should only be used to treat bacterial infections. They do not treat viral infections (e.g., the common cold). When vancomycin is prescribed to treat a bacterial infection, patients should be told that although it is common to feel better early in the course of therapy, the medication should be taken exactly as directed. Skipping doses or not completing the full course of therapy may (1) decrease the effectiveness of the immediate treatment and (2) increase the likelihood that bacteria will develop resistance and will not be treatable by vancomycin or other antibacterial drugs in the future.

Manufactured for:
Xellia Pharmaceuticals USA, LLC
Buffalo Grove, IL 60089
Made in Switzerland

L126USVNC14

PRINCIPAL DISPLAY PANEL - 100 mL Bag Carton - 6 Bag

Rx Only
Sterile

NDC 70594-041-02
Contains six (6) single-dose
Flexible Bags of NDC 70594-041-01

Vancomycin Injection, USP
500 mg per 100 mL (5 mg/mL)

Ready
To Use

For intravenous infusion only. Store below 25°C (77°F), in original package.

Discard unused portion.

xellia
PHARMACEUTICALS

PRINCIPAL DISPLAY PANEL - 100 mL Bag Carton - 12 Bag

Rx Only
Sterile

NDC 70594-041-03
Contains twelve (12) single-dose
Flexible Bags of NDC 70594-041-01

Vancomycin Injection, USP
500 mg per 100 mL (5 mg/mL)

Ready
To Use

For intravenous infusion only. Store below 25°C (77°F), in original package.

Discard unused portion.

xellia
PHARMACEUTICALS

PRINCIPAL DISPLAY PANEL - 200 mL Bag Carton - 6 Bag

Rx Only
Sterile

NDC 70594-042-02
Contains six (6) single-dose
Flexible Bags of NDC 70594-042-01

Vancomycin Injection, USP
1 g per 200 mL (5 mg/mL)

Ready
To Use

For intravenous infusion only. Store below 25°C (77°F), in original package.

Discard unused portion.

xellia
PHARMACEUTICALS

PRINCIPAL DISPLAY PANEL - 200 mL Bag Carton - 12 Bag

Rx Only
Sterile

NDC 70594-042-03
Contains twelve (12) single-dose
Flexible Bags of NDC 70594-042-01

Vancomycin Injection, USP
1 g per 200 mL (5 mg/mL)

Ready
To Use

For intravenous infusion only. Store below 25°C (77°F), in original package.

Discard unused portion.

xellia
PHARMACEUTICALS

PRINCIPAL DISPLAY PANEL - 300 mL Bag Carton

Rx Only
Sterile

NDC 70594-043-02
Contains six (6) single-dose
Flexible Bags of NDC 70594-043-01

Vancomycin Injection, USP
1.5 g per 300 mL (5 mg/mL)

Ready
To Use

For intravenous infusion only. Store below 25°C (77°F), in original package.

Discard unused portion.

xellia
PHARMACEUTICALS

PRINCIPAL DISPLAY PANEL - 400 mL Bag Carton

Rx Only
Sterile

NDC 70594-044-02
Contains six (6) single-dose
Flexible Bags of NDC 70594-044-01

Vancomycin Injection, USP
2 g per 400 mL (5 mg/mL)

Ready
To Use

For intravenous infusion only. Store below 25°C (77°F), in original package.

Discard unused portion.

xellia
PHARMACEUTICALS

PRINCIPAL DISPLAY PANEL - 150 mL Bag Carton - 6 Bag

Rx Only
Sterile

NDC 70594-056-02
Contains six (6) single-dose
Flexible Bags of NDC 70594-056-01

Vancomycin Injection, USP
750 mg per 150 mL (5 mg/mL)

Ready
To Use

For intravenous infusion only. Store below 25°C (77°F), in original package.

Discard unused portion.

xellia
PHARMACEUTICALS

PRINCIPAL DISPLAY PANEL - 150 mL Bag Carton - 12 Bag

Rx Only
Sterile

NDC 70594-056-03
Contains twelve (12) single-dose
Flexible Bags of NDC 70594-056-01

Vancomycin Injection, USP
750 mg per 150 mL (5 mg/mL)

Ready
To Use

For intravenous infusion only. Store below 25°C (77°F), in original package.

Discard unused portion.

xellia
PHARMACEUTICALS

PRINCIPAL DISPLAY PANEL - 250 mL Bag Carton

Rx Only
Sterile

NDC 70594-057-02
Contains six (6) single-dose
Flexible Bags of NDC 70594-057-01

Vancomycin Injection, USP
1.25 g per 250 mL (5 mg/mL)

Ready
To Use

For intravenous infusion only. Store below 25°C (77°F), in original package.

Discard unused portion.

xellia
PHARMACEUTICALS

PRINCIPAL DISPLAY PANEL - 350 mL Bag Carton

Rx Only
Sterile

NDC 70594-058-02
Contains six (6) single-dose
Flexible Bags of NDC 70594-058-01

Vancomycin Injection, USP
1.75 g per 350 mL (5 mg/mL)

Ready
To Use

For intravenous infusion only. Store below 25°C (77°F), in original package.

Discard unused portion.

xellia
PHARMACEUTICALS